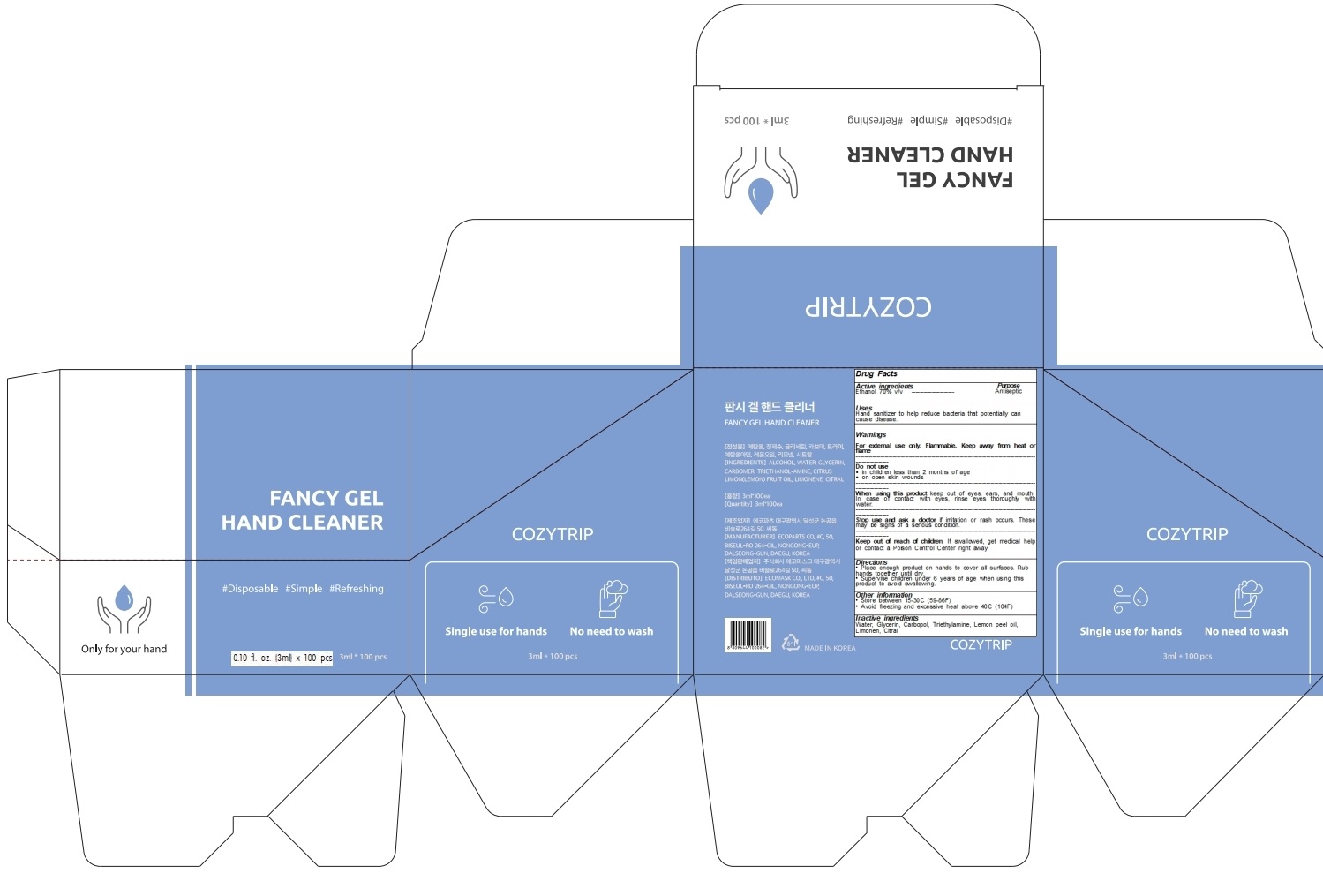 DRUG LABEL: FANCY HAND CLEANER
NDC: 79272-010 | Form: GEL
Manufacturer: Ecoparts
Category: otc | Type: HUMAN OTC DRUG LABEL
Date: 20200629

ACTIVE INGREDIENTS: ALCOHOL 70 mL/100 mL
INACTIVE INGREDIENTS: WATER; Glycerin; CARBOMER HOMOPOLYMER, UNSPECIFIED TYPE; TROLAMINE; LEMON OIL, TERPENELESS; CITRAL

ACTIVE INGREDIENT

Ethanol 70% v/v

INACTIVE INGREDIENTS

Water, Glycerin, Carbopol, Triethylamine, Lemon peel oil, Limonen, Citral

PURPOSE

ANTISEPTIC

WARNINGS

For external use only. Flammable. Keep away from heat or flame

--------------------------------------------------------------------------------------------------------
Do not use
• in children less than 2 months of age
• on open skin wounds
--------------------------------------------------------------------------------------------------------
When using this product keep out of eyes, ears, and mouth. In case of contact with eyes, rinse eyes thoroughly with water.
--------------------------------------------------------------------------------------------------------
Stop use and ask a doctor if irritation or rash occurs. These may be signs of a serious condition.

Keep out of reach of children. If swallowed, get medical help or contact a Poison Control Center right away.

Uses

Hand sanitizer to help reduce bacteria that potentially can cause disease.

Directions

• Place enough product on hands to cover all surfaces. Rub hands together until dry.
• Supervise children under 6 years of age when using this product to avoid swallowing.

Other information

• Store between 15-30C (59-86F)
• Avoid freezing and excessive heat above 40C (104F)